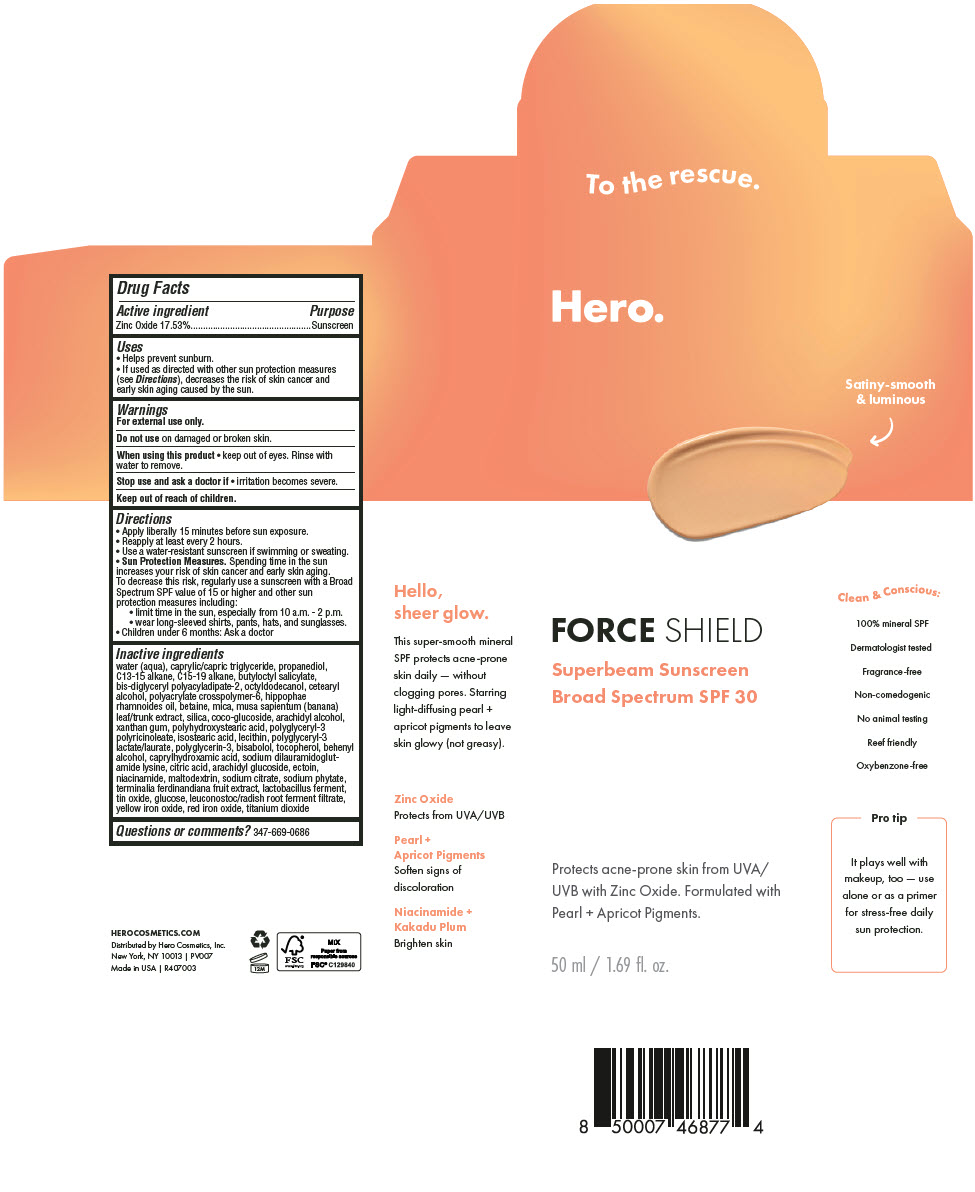 DRUG LABEL: Hero Force Shield Superbeam Sunscreen SPF 30 Apricot
NDC: 10237-004 | Form: LOTION
Manufacturer: Church & Dwight Co., Inc.
Category: otc | Type: HUMAN OTC DRUG LABEL
Date: 20241202

ACTIVE INGREDIENTS: ZINC OXIDE 175.3 mg/1 mL
INACTIVE INGREDIENTS: WATER; MEDIUM-CHAIN TRIGLYCERIDES; PROPANEDIOL; C13-15 ALKANE; C15-19 ALKANE; BUTYLOCTYL SALICYLATE; BIS-DIGLYCERYL POLYACYLADIPATE-2; OCTYLDODECANOL; CETOSTEARYL ALCOHOL; AMMONIUM ACRYLOYLDIMETHYLTAURATE, DIMETHYLACRYLAMIDE, LAURYL METHACRYLATE AND LAURETH-4 METHACRYLATE COPOLYMER, TRIMETHYLOLPROPANE TRIACRYLATE CROSSLINKED (45000 MPA.S); BETAINE; MICA; BANANA; SILICON DIOXIDE; COCO GLUCOSIDE; ARACHIDYL ALCOHOL; XANTHAN GUM; ISOSTEARIC ACID; POLYGLYCERIN-3; LEVOMENOL; TOCOPHEROL; DOCOSANOL; CAPRYLHYDROXAMIC ACID; SODIUM DILAURAMIDOGLUTAMIDE LYSINE; CITRIC ACID MONOHYDRATE; ARACHIDYL GLUCOSIDE; ECTOINE; NIACINAMIDE; MALTODEXTRIN; SODIUM CITRATE, UNSPECIFIED FORM; PHYTATE SODIUM; KAKADU PLUM; STANNIC OXIDE; ANHYDROUS DEXTROSE; LEUCONOSTOC/RADISH ROOT FERMENT FILTRATE; FERRIC OXIDE YELLOW; FERRIC OXIDE RED; TITANIUM DIOXIDE

Hero Force Shield Superbeam Sunscreen SPF 30 Apricot

Drug Facts

Active ingredient

Zinc Oxide 17.53%

Purpose

Sunscreen

Uses

- Helps prevent sunburn.
- If used as directed with other sun protection measures (see Directions), decreases the risk of skin cancer and early skin aging caused by the sun.

Warnings

For external use only.

Do not useon damaged or broken skin.

When using this product

- keep out of eyes. Rinse with water to remove.

Stop use and ask a doctor if

- irritation becomes severe.

Keep out of reach of children.

Directions

- Apply liberally 15 minutes before sun exposure.
- Reapply at least every 2 hours.
- Use a water-resistant sunscreen if swimming or sweating.
- Sun Protection Measures.Spending time in the sun increases your risk of skin cancer and early skin aging. To decrease this risk, regularly use a sunscreen with a Broad Spectrum SPF value of 15 or higher and other sun protection measures including:
  - limit time in the sun, especially from 10 a.m. - 2 p.m.
  - wear long-sleeved shirts, pants, hats, and sunglasses.
- Children under 6 months: Ask a doctor

Inactive ingredients

water (aqua), caprylic/capric triglyceride, propanediol, C13-15 alkane, C15-19 alkane, butyloctyl salicylate, bis-diglyceryl polyacyladipate-2, octyldodecanol, cetearyl alcohol, polyacrylate crosspolymer-6, hippophae rhamnoides oil, betaine, mica, musa sapientum (banana) leaf/trunk extract, silica, coco-glucoside, arachidyl alcohol, xanthan gum, polyhydroxystearic acid, polyglyceryl-3 polyricinoleate, isostearic acid, lecithin, polyglyceryl-3 lactate/laurate, polyglycerin-3, bisabolol, tocopherol, behenyl alcohol, caprylhydroxamic acid, sodium dilauramidoglutamide lysine, citric acid, arachidyl glucoside, ectoin, niacinamide, maltodextrin, sodium citrate, sodium phytate, terminalia ferdinandiana fruit extract, lactobacillus ferment, tin oxide, glucose, leuconostoc/radish root ferment filtrate, yellow iron oxide, red iron oxide, titanium dioxide

Questions or comments?

347-669-0686

Distributed by Hero Cosmetics, Inc.
New York, NY 10013

PRINCIPAL DISPLAY PANEL - 50 ml Tube Box

Hero.

FORCE SHIELD

Superbeam Sunscreen
Broad Spectrum SPF 30

Protects acne-prone skin from UVA/
UVB with Zinc Oxide. Formulated with
Pearl + Apricot Pigments.

50 ml / 1.69 fl. oz.